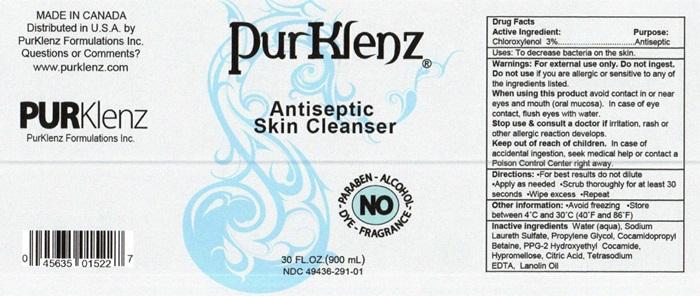 DRUG LABEL: PurKlenz
NDC: 49436-291 | Form: LIQUID
Manufacturer: PurKlenz Formulations Inc.
Category: otc | Type: HUMAN OTC DRUG LABEL
Date: 20251112

ACTIVE INGREDIENTS: CHLOROXYLENOL 2.949 g/100 mL
INACTIVE INGREDIENTS: WATER; SODIUM LAURETH SULFATE; PROPYLENE GLYCOL; COCAMIDOPROPYL BETAINE; PPG-2 HYDROXYETHYL COCAMIDE; HYPROMELLOSES; CITRIC ACID MONOHYDRATE; EDETATE SODIUM; LANOLIN OIL

Active Ingredient

Drug Facts

Active Ingredient:

- Chloroxylenol 3.0%

Purpose

- Antiseptic

Keep out of reach of children. In case of accidental ingestion seek medical help or contact a Poison Control Center right away.

Uses

- To decrease bacteria on the skin

Directions

- For best results do not dilute
- Apply as needed
- Scrub thoroughly for 30 seconds
- Wipe excess with sterile gauze
- Repeat - liquid only
- Massage package and remove towelette - towelette only
- Fold gauze and repeat - towelette only

Other Information

- Reseal container after use - liquid only
- Avoid freezing
- Store between 4° - 30° C (40-86° F)
- Dispose after use - towelette only

Warnings

For external use only
Do not use if you are allergic or sensitive to any of the ingredients listed
When using this product avoid contact in or near eyes and mouth (oral mucosa).
In case of eye contact, flush eyes with water.
Stop and ask a doctor if irritation, rash or other allergic reaction develops.
In case of accidental ingestion seek medical help or contact a Poison Control Center right away.

Inactive Ingredients

Water (aqua), Sodium Laureth Sulfate, Propylene Glycol, Cocamidopropyl Betaine, PPG-2 Hydroxyethyl Cocamide, Hypromellose, Citric Acid, Tetrasodium EDTA, Lanolin Oil

PurKlenz Antiseptic Skin Cleaner Label - 30 FL Oz

PurKlenz®
Antiseptic Skin Cleanser
Chloroxylenol 3.0 % NO PARABEN • ALCOHOL • DYE • FRAGRANCE•Contains No Paraben, Fragrance or Dye
30 FL. OZ. (900 mL)
NDC 49436-291-01
Made in Canada
Distributed in U.S.A. by
PurKlenz Formulations Inc.
Questions or Comments?
www.purklenz.com

PURKlenz

PurKlenz Formulations Inc.